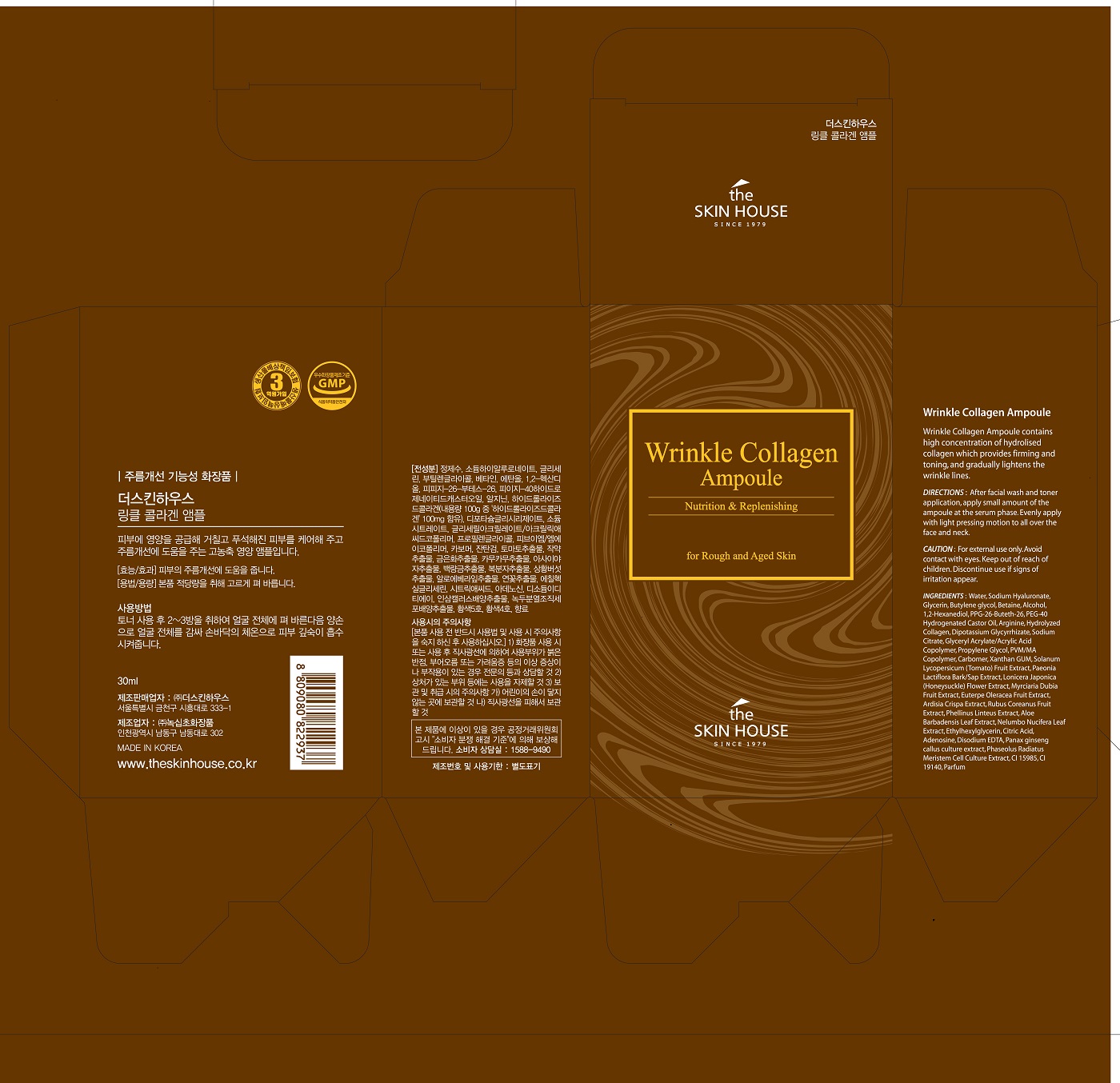 DRUG LABEL: THE SKIN HOUSE WRINKLE COLLAGEN AMPOULE
NDC: 73590-0048 | Form: LIQUID
Manufacturer: NOKSIBCHO cosmetic Co., Ltd.
Category: otc | Type: HUMAN OTC DRUG LABEL
Date: 20200408

ACTIVE INGREDIENTS: ADENOSINE 0.04 g/100 mL
INACTIVE INGREDIENTS: WATER

Drug Facts

ACTIVE INGREDIENT

adenosine

INACTIVE INGREDIENT

Water
Sodium Hyaluronate
Glycerin
Butylene glycol
Betaine
Alcohol
1,2-Hexanediol
PPG-26-Buteth-26
PEG-40 Hydrogenated Castor Oil
Arginine
Hydrolyzed Collagen
Dipotassium Glycyrrhizate
Sodium Citrate
Glyceryl Acrylate/Acrylic Acid Copolymer
Propylene Glycol
PVM/MA Copolymer
Carbomer
Xanthan GUM
Solanum Lycopersicum (Tomato) Fruit Extract
Paeonia Lactiflora Bark/Sap Extract
Lonicera Japonica (Honeysuckle) Flower Extract
Myrciaria Dubia Fruit Extract
Euterpe Oleracea Fruit Extract
Ardisia Crispa Extract
Rubus Coreanus Fruit Extract
Phellinus Linteus Extract
Aloe Barbadensis Leaf Extract
Nelumbo Nucifera Leaf Extract
Citric Acid
Disodium EDTA
Panax ginseng callus culture extract
Phaseolus Radiatus Meristem Cell Culture Extract
Ethylhexylglycerin
CI 15985
CI 19140
Parfum

PURPOSE

wrinkle care

keep out of reach of the children

INDICATIONS AND USAGE

apply proper amount to the skin

WARNINGS

For external use only
When using this product

■ if the following symptoms occurs after use, stop use and consult with a skin specialist

red specks, swelling, itching

■ don’t use on the part where there is injury, eczema, or dermatitis

Keep out of reach of children

■ if swallowed, get medical help or contact a person control center immediately